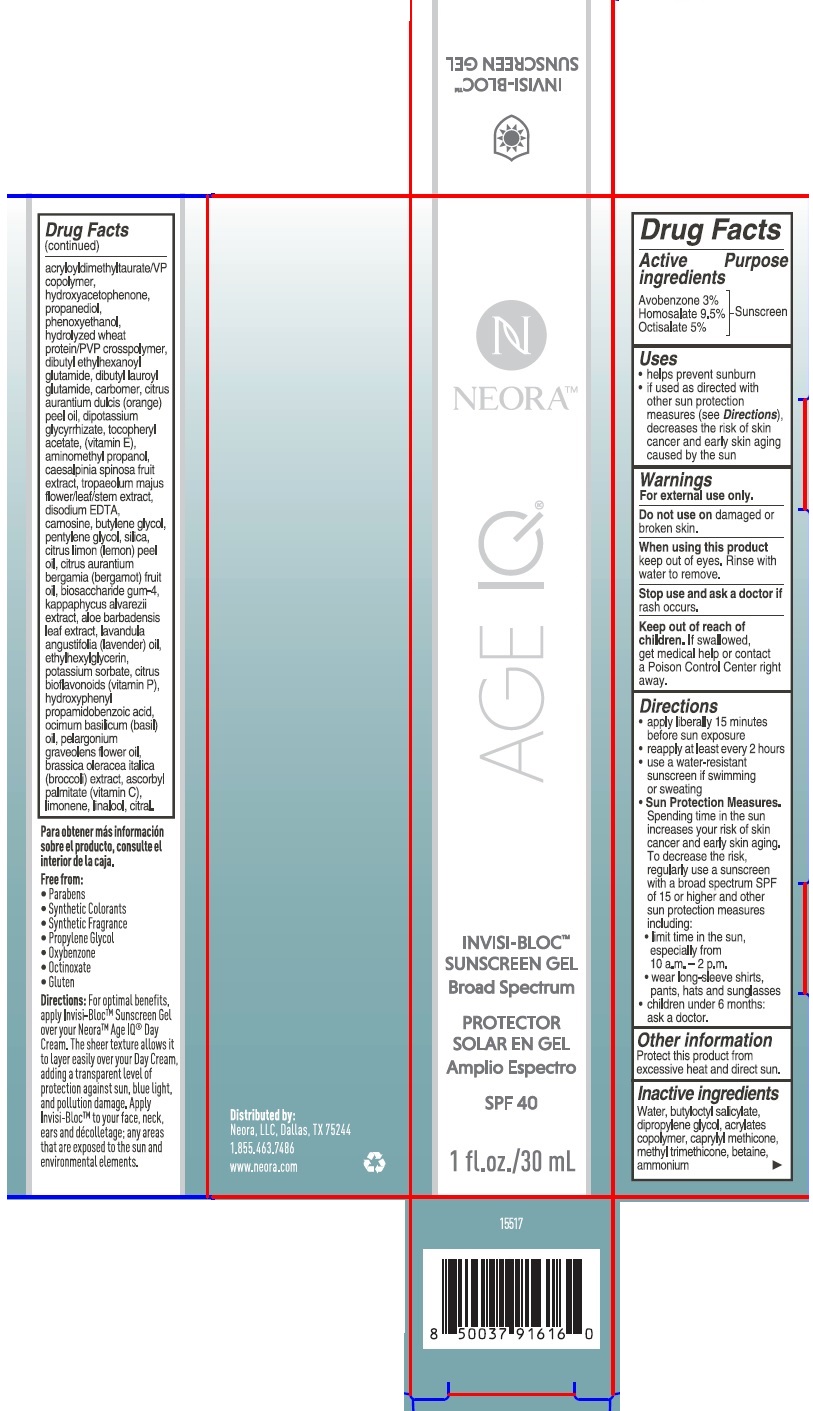 DRUG LABEL: Neora
NDC: 72935-003 | Form: GEL
Manufacturer: Neora, LLC
Category: otc | Type: HUMAN OTC DRUG LABEL
Date: 20231023

ACTIVE INGREDIENTS: OCTISALATE 5 g/100 mL; AVOBENZONE 3 g/100 mL; HOMOSALATE 9.5 g/100 mL
INACTIVE INGREDIENTS: DIPROPYLENE GLYCOL; ASCORBYL PALMITATE; PHENOXYETHANOL; BUTYLOCTYL SALICYLATE; ALPHA-TOCOPHEROL ACETATE; METHYL TRIMETHICONE; BETAINE; PROPANEDIOL; AMMONIUM ACRYLOYLDIMETHYLTAURATE/VP COPOLYMER; HYDROXYACETOPHENONE; HYDROLYZED WHEAT PROTEIN (ENZYMATIC, 3000 MW); DIBUTYL ETHYLHEXANOYL GLUTAMIDE; DIBUTYL LAUROYL GLUTAMIDE; CARBOMER HOMOPOLYMER, UNSPECIFIED TYPE; AMINOMETHYLPROPANOL; CAESALPINIA SPINOSA FRUIT POD; BUTYLENE GLYCOL; EDETATE DISODIUM; CARNOSINE; SILICON DIOXIDE; BIOSACCHARIDE GUM-4; KAPPAPHYCUS ALVAREZII; ALOE VERA LEAF; LAVENDER OIL; ETHYLHEXYLGLYCERIN; POTASSIUM SORBATE; CITRUS BIOFLAVONOIDS; WATER; HYDROXYPHENYL PROPAMIDOBENZOIC ACID; PELARGONIUM GRAVEOLENS FLOWER OIL; LEMON OIL; LINALOOL, (+/-)-; TROPAEOLUM MAJUS FLOWER; CITRAL; GLYCYRRHIZINATE DIPOTASSIUM; LUVISET 360; BROCCOLI; ORANGE OIL; BERGAMOT OIL; CAPRYLYL TRISILOXANE; PENTYLENE GLYCOL; LIMONENE, (+)-; BASIL OIL

Neora Age IQ INVISI-BLOC Sunscreen Gel

Active ingredients

Avobenzone 3%

Homosalate 9.5%

Octisalate 5%

Purpose

Sunscreen

Uses

- helps prevent sunburn
- if used as directed with other sun protection measures (see Directions), decreases the risk of skin cancer and early skin aging caused by the sun

Warnings

For external use only.

Do not use on damaged or broken skin

When using this product keep out of eyes. Rinse with water to remove.

Stop use and ask a doctor if rash occurs

Keep out of reach of children. If swallowed, get medical help or contact a Poison Control Center right away.

Directions

- apply liberally 15 minutes before sun exposure.
- reapply at least every 2 hours
- use a water resistant sunscreen if swimming or sweating
- Sun Protection Measures. Spending time in the sun increases your risk of skin cancer and early skin aging. To decrease this risk, regularly use a sunscreen with a Broad Spectrum SPF value of 15 or higher and other sun protection measures including:
- limit time in the sun, especially from 10.a.m. - 2 p.m.
- wear long-sleeved shirts, pants, hats and sunglasses
- children under 6 months: ask a doctor

Other information

Protect this product from excessive heat and direct sun.

Inactive ingredients

Water, butyloctyl salicylate, dipropylene glycol, acrylates copolymer, caprylyl methicone, methyl trimethicone, betaine, ammonium, acryloyldimethyltaurate/VP copolymer, hydroxyacetophenone, propanediol, phenoxyethanol, hyrolyzed wheat protein/PVP crosspolymer, dibutyl ethylhexanoyl glutamide, dibutyl lauroyl glutamide, carbomer, citrus aurantium dilcis (orange) peel oil, dipotassium glycyrrhizate, tocopheryl acetate, (vitamin E), aminomethyl propanol, caesalpinia spinosa fruit extract, tropaeolum majus flower/leaf/stem extract, disodium EDTA, carnosine, butylene glycol, pentylene glycol, silica, citrus limon (lemon) peel oil, citrus aurantium bergamia (bergamot) fruit oil, biosaccharide gum-4, kappaphycus alvarezii extract, aloe barbadensis leaf extract, lavandula angustifolia (lavender) oil, ethylhexylglycerin, potassium sorbate, citrus bioflavonoids (vitamin P), hydroxyphenyl propamidobenzoic acid, ocimum basilicum (basil) oil, pelargonium graveolens flower oil, brassica oleracea italica (broccoli) extract, ascorbyl palmitate (vitamin C), limonene, linalool, citral.

Distributed by:

Neora, LLC, Dallas, TX 75244

1.855.463.7486

www.neora.com

PACKAGE LABEL

NEORA™

AGE IQ

INVISI-BLOC™

SUNSCREEN GEL

Broad Spectrum SPF 40

1 fl. oz. / 30 mL